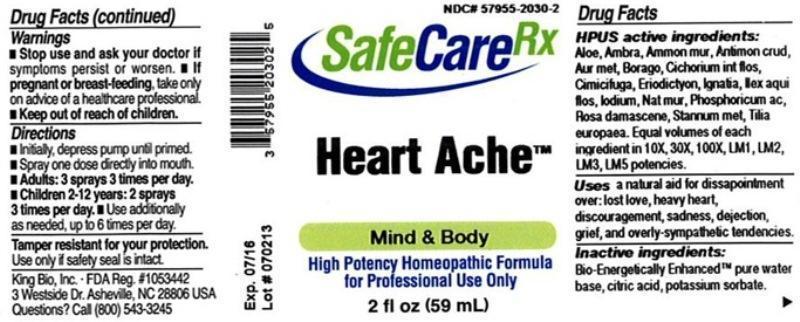 DRUG LABEL: Heart Ache
NDC: 57955-2030 | Form: LIQUID
Manufacturer: King Bio Inc.
Category: homeopathic | Type: HUMAN OTC DRUG LABEL
Date: 20130812

ACTIVE INGREDIENTS: ALOE 10 [hp_X]/59 mL; AMBERGRIS 10 [hp_X]/59 mL; AMMONIUM CHLORIDE 10 [hp_X]/59 mL; ANTIMONY TRISULFIDE 10 [hp_X]/59 mL; GOLD 10 [hp_X]/59 mL; BORAGE 10 [hp_X]/59 mL; CICHORIUM INTYBUS FLOWER 10 [hp_X]/59 mL; BLACK COHOSH 10 [hp_X]/59 mL; ERIODICTYON CALIFORNICUM LEAF 10 [hp_X]/59 mL; STRYCHNOS IGNATII SEED 10 [hp_X]/59 mL; ILEX AQUIFOLIUM FLOWERING TOP 10 [hp_X]/59 mL; IODINE 10 [hp_X]/59 mL; SODIUM CHLORIDE 10 [hp_X]/59 mL; PHOSPHORIC ACID 10 [hp_X]/59 mL; ROSA DAMASCENA FLOWERING TOP 10 [hp_X]/59 mL; TIN 10 [hp_X]/59 mL; TILIA X EUROPAEA FLOWER 10 [hp_X]/59 mL
INACTIVE INGREDIENTS: WATER; CITRIC ACID MONOHYDRATE; POTASSIUM SORBATE

Heart Ache™

Drug Facts

____________________________________________________________________________________________________________

HPUS active ingredients: Aloe socotrina, Ambra grisea, Ammonium muriaticum, Antimonium crudum, Aurum metallicum, Borago officinalis, Cichorium intybus, flos, Cimicifuga racemosa, Eriodictyon californicum, Ignatia amara, Ilex aquifolium, flos, Iodium, Natrum muriaticum, Phosphoricum acidum, Rosa damascena, Stannum metallicum, Tilia europaea. Equal volumes of each ingredient in 10X, 30X, 100X, LM1, LM2, LM3, LM5 potencies.

INDICATIONS AND USAGE

Uses a natural aid for dissapointment over:

- lost love
- heavy heart
- discouragement
- sadness
- dejection
- grief
- overly-sympathetic tendencies

INACTIVE INGREDIENT

Inactive ingredients: Bio-Energetically Enhanced pure water base, citric acid, potassium sorbate.

Warnings

- Stop use and ask your doctor if symptoms persist or worsen.
- If pregnant or breast-feeding, take only on advice of a healthcare professional.

- Keep out of reach of children.

Directions:

- Initially, depress pump until primed.
- Spray one dose directly into mouth.
- Adults: 3 sprays 3 times per day.
- Children 2-12 years: 2 sprays 3 times per day.
- Use additionally as needed, up to 6 times per day.

OTHER SAFETY INFORMATION

Tamper resistant for your protection. Use only if safety seal is intact.

PURPOSE

Uses a natural aid for dissapointment over: lost love, heavy heart, discouragement, sadness, dejection, grief, and overly-sympathetic tendencies.